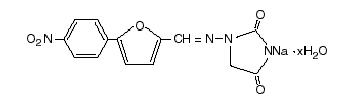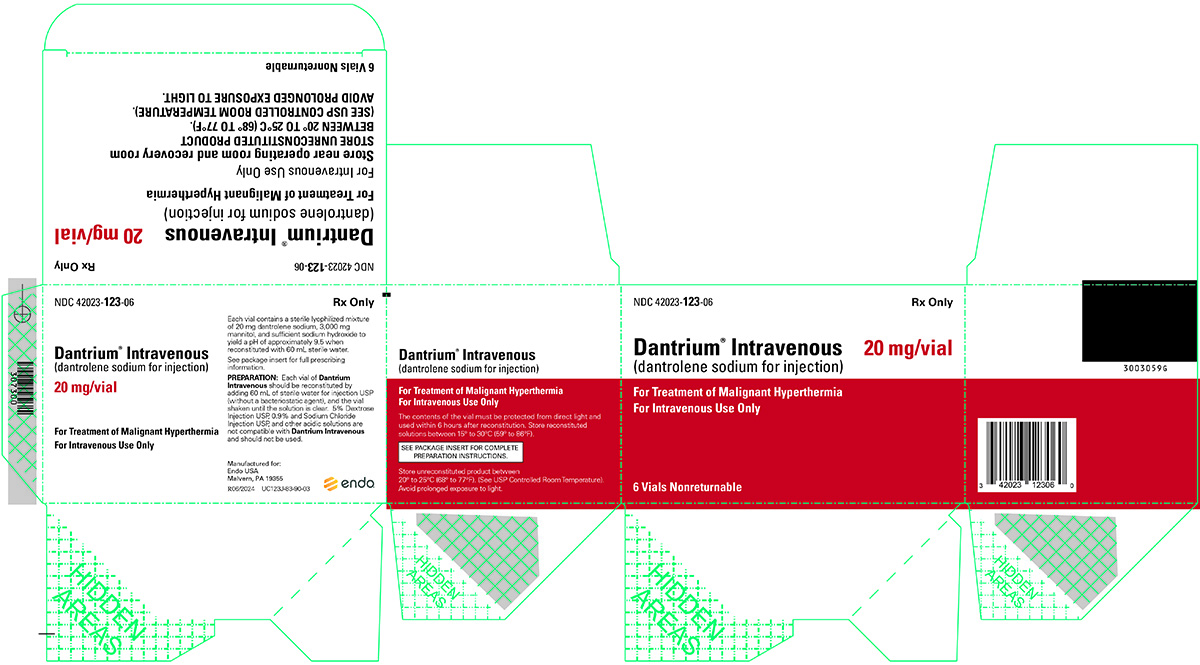 DRUG LABEL: Dantrium
NDC: 42023-123 | Form: INJECTION
Manufacturer: Par Health USA, LLC
Category: prescription | Type: HUMAN PRESCRIPTION DRUG LABEL
Date: 20240624

ACTIVE INGREDIENTS: DANTROLENE SODIUM 20 mg/60 mL
INACTIVE INGREDIENTS: MANNITOL; SODIUM HYDROXIDE

Dantrium® Intravenous (dantrolene sodium for injection)

DESCRIPTION:

Dantrium Intravenous is a sterile, non-pyrogenic, lyophilized formulation of dantrolene sodium for injection. Dantrium Intravenous is supplied in 70 mL vials containing 20 mg dantrolene sodium, 3000 mg mannitol, and sufficient sodium hydroxide to yield a pH of approximately 9.5 when reconstituted with 60 mL sterile water for injection USP (without a bacteriostatic agent).

Dantrium is classified as a direct-acting skeletal muscle relaxant. Chemically, Dantrium is hydrated 1-[[[5-(4-nitrophenyl)-2-furanyl]methylene]amino]-2,4-imidazolidinedione sodium salt. The structural formula for the hydrated salt is:

The hydrated salt contains approximately 15% water (3-1/2 moles) and has a molecular weight of 399. The anhydrous salt (dantrolene) has a molecular weight of 336.

CLINICAL PHARMACOLOGY:

In isolated nerve-muscle preparation, Dantrium has been shown to produce relaxation by affecting the contractile response of the muscle at a site beyond the myoneural junction. In skeletal muscle, Dantrium dissociates the excitation-contraction coupling, probably by interfering with the release of Ca++ from the sarcoplasmic reticulum. The administration of intravenous Dantrium to human volunteers is associated with loss of grip strength and weakness in the legs, as well as subjective CNS complaints (see also PRECAUTIONS, Information for Patients). Information concerning the passage of Dantrium across the blood-brain barrier is not available.

In the anesthetic-induced malignant hyperthermia syndrome, evidence points to an intrinsic abnormality of skeletal muscle tissue. In affected humans, it has been postulated that "triggering agents" (e.g., general anesthetics and depolarizing neuromuscular blocking agents) produce a change within the cell which results in an elevated myoplasmic calcium. This elevated myoplasmic calcium activates acute cellular catabolic processes that cascade to the malignant hyperthermia crisis.

It is hypothesized that addition of Dantrium to the "triggered" malignant hyperthermic muscle cell reestablishes a normal level of ionized calcium in the myoplasm. Inhibition of calcium release from the sarcoplasmic reticulum by Dantrium reestablishes the myoplasmic calcium equilibrium, increasing the percentage of bound calcium. In this way, physiologic, metabolic, and biochemical changes associated with the malignant hyperthermia crisis may be reversed or attenuated. Experimental results in malignant hyperthermia susceptible swine show that prophylactic administration of intravenous or oral dantrolene prevents or attenuates the development of vital sign and blood gas changes characteristic of malignant hyperthermia in a dose related manner. The efficacy of intravenous dantrolene in the treatment of human and porcine malignant hyperthermia crisis, when considered along with prophylactic experiments in malignant hyperthermia susceptible swine, lends support to prophylactic use of oral or intravenous dantrolene in malignant hyperthermia susceptible humans. When prophylactic intravenous dantrolene is administered as directed, whole blood concentrations remain at a near steady state level for 3 or more hours after the infusion is completed. Clinical experience has shown that early vital sign and/or blood gas changes characteristic of malignant hyperthermia may appear during or after anesthesia and surgery despite the prophylactic use of dantrolene and adherence to currently accepted patient management practices. These signs are compatible with attenuated malignant hyperthermia and respond to the administration of additional intravenous dantrolene (see DOSAGE AND ADMINISTRATION). The administration of the recommended prophylactic dose of intravenous dantrolene to healthy volunteers was not associated with clinically significant cardiorespiratory changes.

Specific metabolic pathways for the degradation and elimination of Dantrium in humans have been established. Dantrolene is found in measurable amounts in blood and urine. Its major metabolites in body fluids are 5-hydroxy dantrolene and an acetylamino metabolite of dantrolene. Another metabolite with an unknown structure appears related to the latter. Dantrium may also undergo hydrolysis and subsequent oxidation forming nitrophenylfuroic acid.

The mean biologic half-life of Dantrium after intravenous administration is variable, between 4 to 8 hours under most experimental conditions. Based on assays of whole blood and plasma, slightly greater amounts of dantrolene are associated with red blood cells than with the plasma fraction of blood. Significant amounts of dantrolene are bound to plasma proteins, mostly albumin, and this binding is readily reversible.

Cardiopulmonary depression has not been observed in malignant hyperthermia susceptible swine following the administration of up to 7.5 mg/kg intravenous dantrolene. This is twice the amount needed to maximally diminish twitch response to single supramaximal peripheral nerve stimulation (95% inhibition). A transient, inconsistent, depressant effect on gastrointestinal smooth muscles has been observed at high doses.

INDICATIONS AND USAGE:

Dantrium Intravenous is indicated, along with appropriate supportive measures, for the management of the fulminant hypermetabolism of skeletal muscle characteristic of malignant hyperthermia crises in patients of all ages. Dantrium Intravenous should be administered by continuous rapid intravenous push as soon as the malignant hyperthermia reaction is recognized (i.e., tachycardia, tachypnea, central venous desaturation, hypercarbia, metabolic acidosis, skeletal muscle rigidity, increased utilization of anesthesia circuit carbon dioxide absorber, cyanosis and mottling of the skin, and, in many cases, fever).

Dantrium Intravenous is also indicated preoperatively, and sometimes postoperatively, to prevent or attenuate the development of clinical and laboratory signs of malignant hyperthermia in individuals judged to be malignant hyperthermia susceptible.

CONTRAINDICATIONS:

None.

WARNINGS:

The use of Dantrium Intravenous in the management of malignant hyperthermia crisis is not a substitute for previously known supportive measures. These measures must be individualized, but it will usually be necessary to discontinue the suspect triggering agents, attend to increased oxygen requirements, manage the metabolic acidosis, institute cooling when necessary, monitor urinary output, and monitor for electrolyte imbalance.

Since the effect of disease state and other drugs on Dantrium-related skeletal muscle weakness, including possible respiratory depression, cannot be predicted, patients who receive Dantrium Intravenous preoperatively should have vital signs monitored.

If patients judged malignant hyperthermia susceptible are administered intravenous or oral Dantrium preoperatively, anesthetic preparation must still follow a standard malignant hyperthermia susceptible regimen, including the avoidance of known triggering agents. Monitoring for early clinical and metabolic signs of malignant hyperthermia is indicated because attenuation of malignant hyperthermia, rather than prevention, is possible. These signs usually call for the administration of additional intravenous dantrolene.

PRECAUTIONS:

General:

Care must be taken to prevent extravasation of Dantrium Intravenous solution into the surrounding tissues due to the high pH of the intravenous formulation and potential for tissue necrosis.

When mannitol is used for prevention or treatment of late renal complications of malignant hyperthermia, the 3 g of mannitol needed to dissolve each 20 mg vial of Dantrium Intravenous should be taken into consideration.

Information for Patients:

Based upon data in human volunteers, perioperatively, it is appropriate to tell patients who receive Dantrium Intravenous that symptoms of muscle weakness should be expected postoperatively (i.e., decrease in grip strength and weakness of leg muscles, especially walking down stairs). In addition, symptoms such as "lightheadedness" may be noted. Since some of these symptoms may persist for up to 48 hours, patients must not operate an automobile or engage in other hazardous activity during this time. Caution is also indicated at meals on the day of administration because difficulty swallowing and choking has been reported. Caution should be exercised in the concomitant administration of tranquilizing agents.

Drug Interactions:

Dantrium is metabolized by the liver, and it is theoretically possible that its metabolism may be enhanced by drugs known to induce hepatic microsomal enzymes. However, neither phenobarbital nor diazepam appears to affect Dantrium metabolism. Binding to plasma protein is not significantly altered by diazepam, diphenylhydantoin, or phenylbutazone. Binding to plasma proteins is reduced by warfarin and clofibrate and increased by tolbutamide.

Cardiovascular collapse in association with marked hyperkalemia has been reported in patients receiving dantrolene in combination with calcium channel blockers. It is recommended that the combination of intravenous dantrolene sodium and calcium channel blockers, such as verapamil, not be used together during the management of malignant hyperthermia crisis.

Administration of dantrolene may potentiate vecuronium-induced neuromuscular block.

Carcinogenesis, Mutagenesis, and Impairment of Fertility:

Sprague-Dawley female rats fed Dantrium for 18 months at dosage levels of 15, 30, and 60 mg/kg/day showed an increased incidence of benign and malignant mammary tumors compared with concurrent controls. At the highest dose level (approximately the same as the maximum recommended daily dose on a mg/m^2 basis), there was an increase in the incidence of benign hepatic lymphatic neoplasms. In a 30-month study in Sprague-Dawley rats fed dantrolene sodium, the highest dose level (approximately the same as the maximum recommended daily dose on a mg/m^2 basis) produced a decrease in the time of onset of mammary neoplasms. Female rats at the highest dose level showed an increased incidence of hepatic lymphangiomas and hepatic angiosarcomas.

The only drug-related effect seen in a 30-month study in Fischer-344 rats was a dose-related reduction in the time of onset of mammary and testicular tumors. A 24-month study in HaM/ICR mice revealed no evidence of carcinogenic activity.

The significance of carcinogenicity data relative to use of Dantrium in humans is unknown.

Dantrolene sodium has produced positive results in the Ames S. Typhimurium bacterial mutagenesis assay in the presence and absence of a liver activating system.

Dantrolene sodium administered to male and female rats at dose levels up to 45 mg/kg/day (approximately 1.4 times the maximum recommended daily dose on a mg/m^2 basis) showed no adverse effects on fertility or general reproductive performance.

Pregnancy:

Pregnancy Category C:

Dantrium has been shown to be embryocidal in the rabbit and has been shown to decrease pup survival in the rat when given at doses seven times the human oral dose. There are no adequate and well-controlled studies in pregnant women. Dantrium Intravenous should be used during pregnancy only if the potential benefit justifies the potential risk to the fetus.

Labor and Delivery:

In one uncontrolled study, 100 mg per day of prophylactic oral Dantrium was administered to term pregnant patients awaiting labor and delivery. Dantrolene readily crossed the placenta, with maternal and fetal whole blood levels approximately equal at delivery; neonatal levels then fell approximately 50% per day for 2 days before declining sharply. No neonatal respiratory and neuromuscular side effects were detected at low dose. More data, at higher doses, are needed before more definitive conclusions can be made.

Nursing Mothers:

Dantrolene has been detected in human milk at low concentrations (less than 2 micrograms per mL) during repeat intravenous administration over 3 days. Because of the potential for serious adverse reactions in nursing infants from dantrolene, a decision should be made whether to discontinue nursing or to discontinue the drug, taking into account the importance of the drug to the mother.

Geriatric Use:

Clinical studies of Dantrium Intravenous did not include sufficient numbers of subjects aged 65 and over to determine whether they respond differently from younger subjects. Other reported clinical experience has not identified differences in responses between the elderly and younger patients. In general, dose selection for an elderly patient should be cautious reflecting the greater frequency of decreased hepatic, renal, or cardiac function, and of concomitant disease or other drug therapy.

ADVERSE REACTIONS:

There have been occasional reports of death following malignant hyperthermia crisis even when treated with intravenous dantrolene; incidence figures are not available (the pre-dantrolene mortality of malignant hyperthermia crisis was approximately 50%). Most of these deaths can be accounted for by late recognition, delayed treatment, inadequate dosage, lack of supportive therapy, intercurrent disease and/or the development of delayed complications such as renal failure or disseminated intravascular coagulopathy. In some cases there are insufficient data to completely rule out therapeutic failure of dantrolene.

There are reports of fatality in malignant hyperthermia crisis, despite initial satisfactory response to intravenous dantrolene, which involve patients who could not be weaned from dantrolene after initial treatment.

The administration of Dantrium Intravenous to human volunteers is associated with loss of grip strength and weakness in the legs, as well as drowsiness and dizziness.

The following adverse reactions are in approximate order of severity:

There are rare reports of pulmonary edema developing during the treatment of malignant hyperthermia crisis in which the diluent volume and mannitol needed to deliver intravenous dantrolene possibly contributed.

There have been reported cases of hepatotoxicity following the use of intravenous dantrolene products. Elevated liver enzymes have occurred hours to days following use of intravenous dantrolene, though many of these cases were observed in patients with comorbidities (e.g., critical illness).

There have been reports of thrombophlebitis following administration of intravenous dantrolene; actual incidence figures are not available. Tissue necrosis secondary to extravasation has been reported.

There have been rare reports of urticaria and erythema possibly associated with the administration of Dantrium Intravenous. There has been one case of anaphylaxis.

Injection site reactions (pain, erythema, swelling), commonly due to extravasation, have been reported.

The following events have been reported in patients receiving oral dantrolene: aplastic anemia, leukopenia, lymphocytic lymphoma, and heart failure. (See package insert for Dantrium (dantrolene sodium) Capsules for a complete listing of adverse reactions.)

The published literature has included some reports of Dantrium use in patients with Neuroleptic Malignant Syndrome (NMS). Dantrium Intravenous is not indicated for the treatment of NMS and patients may expire despite treatment with Dantrium Intravenous.

For medical advice about adverse reactions contact your medical professional. To report SUSPECTED ADVERSE REACTIONS, contact Endo at 1-800-828-9393 or FDA at 1-800-FDA-1088 or www.fda.gov/medwatch.

OVERDOSAGE:

Because Dantrium Intravenous must be administered at a low concentration in a large volume of fluid, acute toxicity of Dantrium Intravenous could not be assessed in animals. In 14-day (subacute) studies, the intravenous formulation of Dantrium was relatively non-toxic to rats at doses of 10 mg/kg/day and 20 mg/kg/day. While 10 mg/kg/day in dogs for 14 days evoked little toxicity, 20 mg/kg/day for 14 days caused hepatic changes of questionable biologic significance.

Symptoms which may occur in case of overdose include, but are not limited to, muscular weakness and alterations in the state of consciousness (e.g., lethargy, coma), vomiting, diarrhea, and crystalluria.

For acute overdosage, general supportive measures should be employed.

Intravenous fluids should be administered in fairly large quantities to avert the possibility of crystalluria. An adequate airway should be maintained and artificial resuscitation equipment should be at hand. Electrocardiographic monitoring should be instituted, and the patient carefully observed. The value of dialysis in Dantrium overdose is not known.

DOSAGE AND ADMINISTRATION:

As soon as the malignant hyperthermia reaction is recognized, all anesthetic agents should be discontinued; the administration of 100% oxygen is recommended. Dantrium Intravenous should be administered by continuous rapid intravenous push beginning at a minimum dose of 1 mg/kg, and continuing until symptoms subside or the maximum cumulative dose of 10 mg/kg has been reached.

If the physiologic and metabolic abnormalities reappear, the regimen may be repeated. It is important to note that administration of Dantrium Intravenous should be continuous until symptoms subside. The effective dose to reverse the crisis is directly dependent upon the individual's degree of susceptibility to malignant hyperthermia, the amount and time of exposure to the triggering agent, and the time elapsed between onset of the crisis and initiation of treatment.

Pediatric Dose:

Experience to date indicates that the dose of Dantrium Intravenous for pediatric patients is the same as for adults.

Preoperatively:

Dantrium Intravenous and/or Dantrium Capsules may be administered preoperatively to patients judged malignant hyperthermia susceptible as part of the overall patient management to prevent or attenuate the development of clinical and laboratory signs of malignant hyperthermia.

Dantrium Intravenous: The recommended prophylactic dose of Dantrium Intravenous is 2.5 mg/kg, starting approximately 1-1/4 hours before anticipated anesthesia and infused over approximately 1 hour. This dose should prevent or attenuate the development of clinical and laboratory signs of malignant hyperthermia provided that the usual precautions, such as avoidance of established malignant hyperthermia triggering agents, are followed.

Additional Dantrium Intravenous may be indicated during anesthesia and surgery because of the appearance of early clinical and/or blood gas signs of malignant hyperthermia or because of prolonged surgery (see also CLINICAL PHARMACOLOGY, WARNINGS, and PRECAUTIONS). Additional doses must be individualized.

Oral Administration of Dantrium Capsules:

Administer 4 to 8 mg/kg/day of oral Dantrium Capsules in three or four divided doses for 1 or 2 days prior to surgery, with the last dose being given with a minimum of water approximately 3 to 4 hours before scheduled surgery. Adjustment can usually be made within the recommended dosage range to avoid incapacitation (weakness, drowsiness, etc.) or excessive gastrointestinal irritation (nausea and/or vomiting). See also the package insert for Dantrium Capsules.

Post Crisis Follow-Up:

Dantrium Capsules, 4 to 8 mg/kg/day, in four divided doses should be administered for 1 to 3 days following a malignant hyperthermia crisis to prevent recurrence of the manifestations of malignant hyperthermia.

Dantrium Intravenous may be used postoperatively to prevent or attenuate the recurrence of signs of malignant hyperthermia when oral administration of Dantrium Capsules is not practical. The dose of Dantrium Intravenous in the postoperative period must be individualized, starting with 1 mg/kg or more as the clinical situation dictates.

PREPARATION:

Each vial of Dantrium Intravenous should be reconstituted by adding 60 mL of sterile water for injection USP (without a bacteriostatic agent), and the vial shaken until the solution is clear. 5% Dextrose Injection USP, 0.9% Sodium Chloride Injection USP, and other acidic solutions are not compatible with Dantrium Intravenous and should not be used. The contents of the vial must be protected from direct light and used within 6 hours after reconstitution. Store reconstituted solutions between 15° to 30°C (59° to 86°F).

Reconstituted Dantrium Intravenous should not be transferred to large glass bottles for prophylactic infusion due to precipitate formation observed with the use of some glass bottles as reservoirs.

For prophylactic infusion, the required number of individual vials of Dantrium Intravenous should be reconstituted as outlined above. The contents of individual vials are then transferred to a larger volume sterile intravenous plastic bag. Stability data on file at Endo indicate commercially available sterile plastic bags are acceptable drug delivery devices. However, it is recommended that the prepared infusion be inspected carefully for cloudiness and/or precipitation prior to dispensing and administration. Such solutions should not be used. While stable for 6 hours, it is recommended that the infusion be prepared immediately prior to the anticipated dosage administration time.

Parenteral drug products should be inspected visually for particulate matter and discoloration prior to administration.

HOW SUPPLIED:

Dantrium Intravenous (NDC 42023-123-06) is available in vials containing a sterile lyophilized mixture of 20 mg dantrolene sodium, 3000 mg mannitol, and sufficient sodium hydroxide to yield a pH of approximately 9.5 when reconstituted with 60 mL sterile water for injection USP (without a bacteriostatic agent).

STORAGE AND HANDLING

Store unreconstituted product between 20° to 25°C (68° to 77°F). (See USP Controlled Room Temperature). Avoid prolonged exposure to light.

Rx only.

Manufactured for:

Endo USA

Malvern, PA 19355

© 2024 Endo, Inc. or one of its affiliates.

Revised: 06/2024

PRINCIPAL DISPLAY PANEL - 20 mg Vial Carton

6 Vials Nonreturnable
NDC 42023-123-06

20 mg

Dantrium® Intravenous
(dantrolene sodium for injection)

For treatment of malignant hyperthermia
FOR INTRAVENOUS USE ONLY

Rx Only